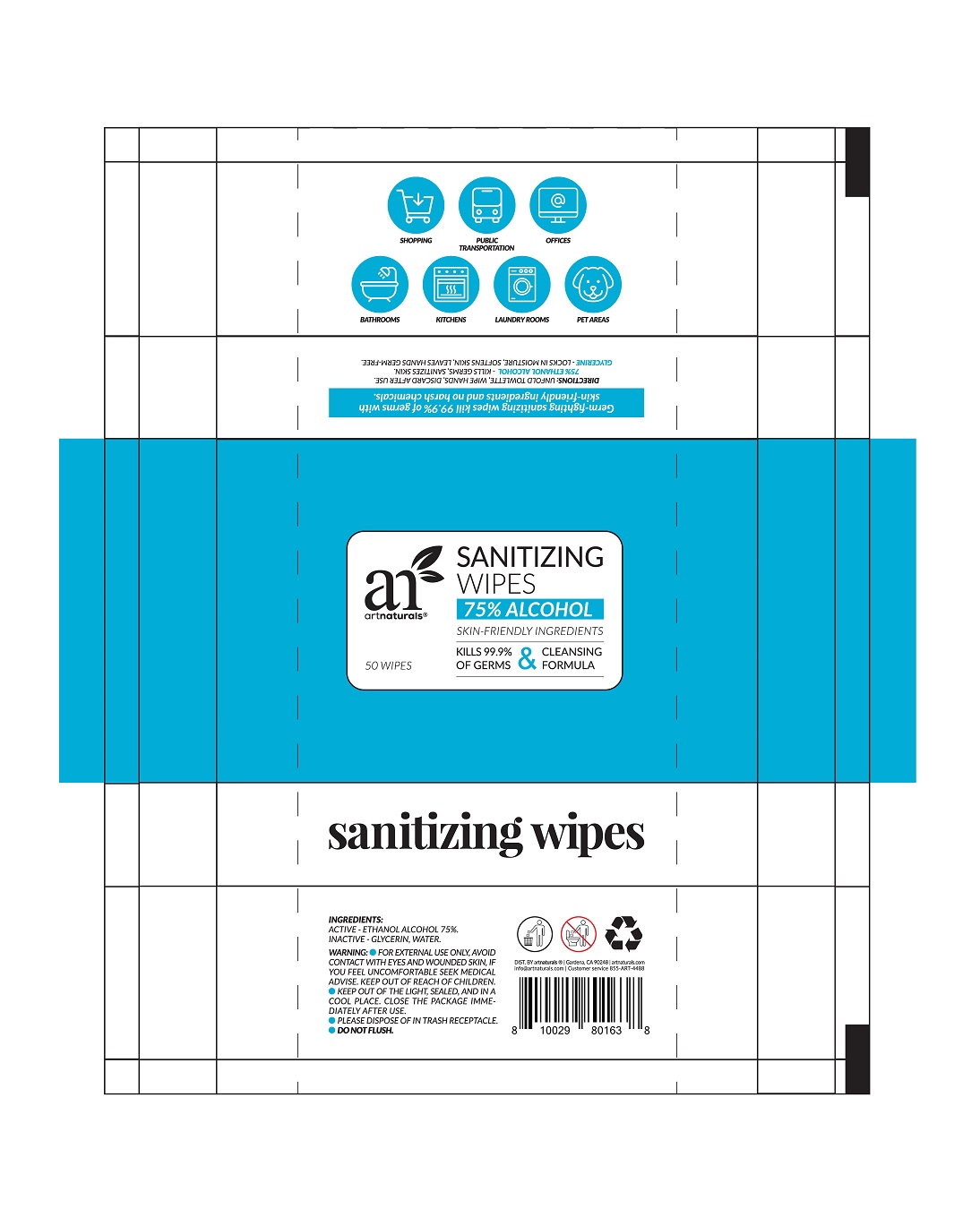 DRUG LABEL: Sanitizing Wipes
NDC: 75163-201 | Form: PATCH
Manufacturer: Zhuji Jianhe Paper Co., Ltd
Category: otc | Type: HUMAN OTC DRUG LABEL
Date: 20200508

ACTIVE INGREDIENTS: ALCOHOL 0.75 U/1 U
INACTIVE INGREDIENTS: WATER; GLYCERIN

JianHe, Sanitizing Wipes, 75% Alcohol, *50 wipes

Active ingredient

Ethanol Alcohol, 75% v/v.

Inactive ingredient

Glycerin, Water.

Purpose

Daily Clean.

Kill germs, sanitizes skin.

When using

Avoid contact with eyes and wounded skin.

If you feel uncomfortable seek medical advise.

Do not use on wounded skin.

Stop use

Stop use if you feel uncomfortable and seek medical advise.

Keep out of reach of children

Indications & usage

Kill germs and sanitizes skin.

Dosage & administration

Unfold towlette, wipe hands, discard after use.

For external use only.

Warnings

For external use only, avoid contact with eyes and wounded skin, if you feel uncomfortable seek medical advise.

Other information

- Keep out of the light, sealed, and in a cool place. Close the package immediately after use.
- Please dispose of in trash receptacle.
- Do Not Flush.